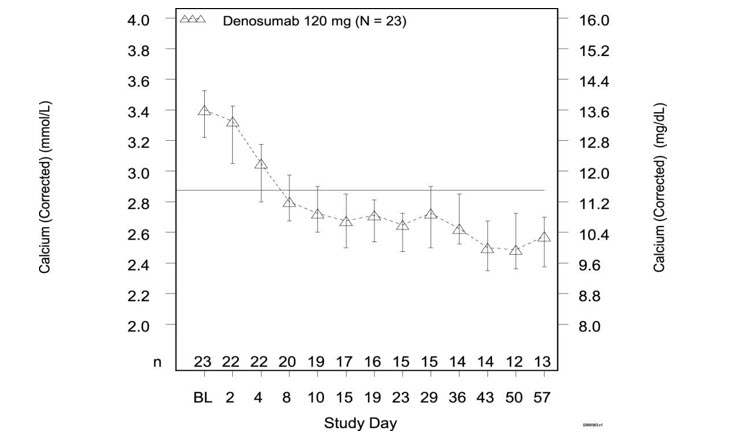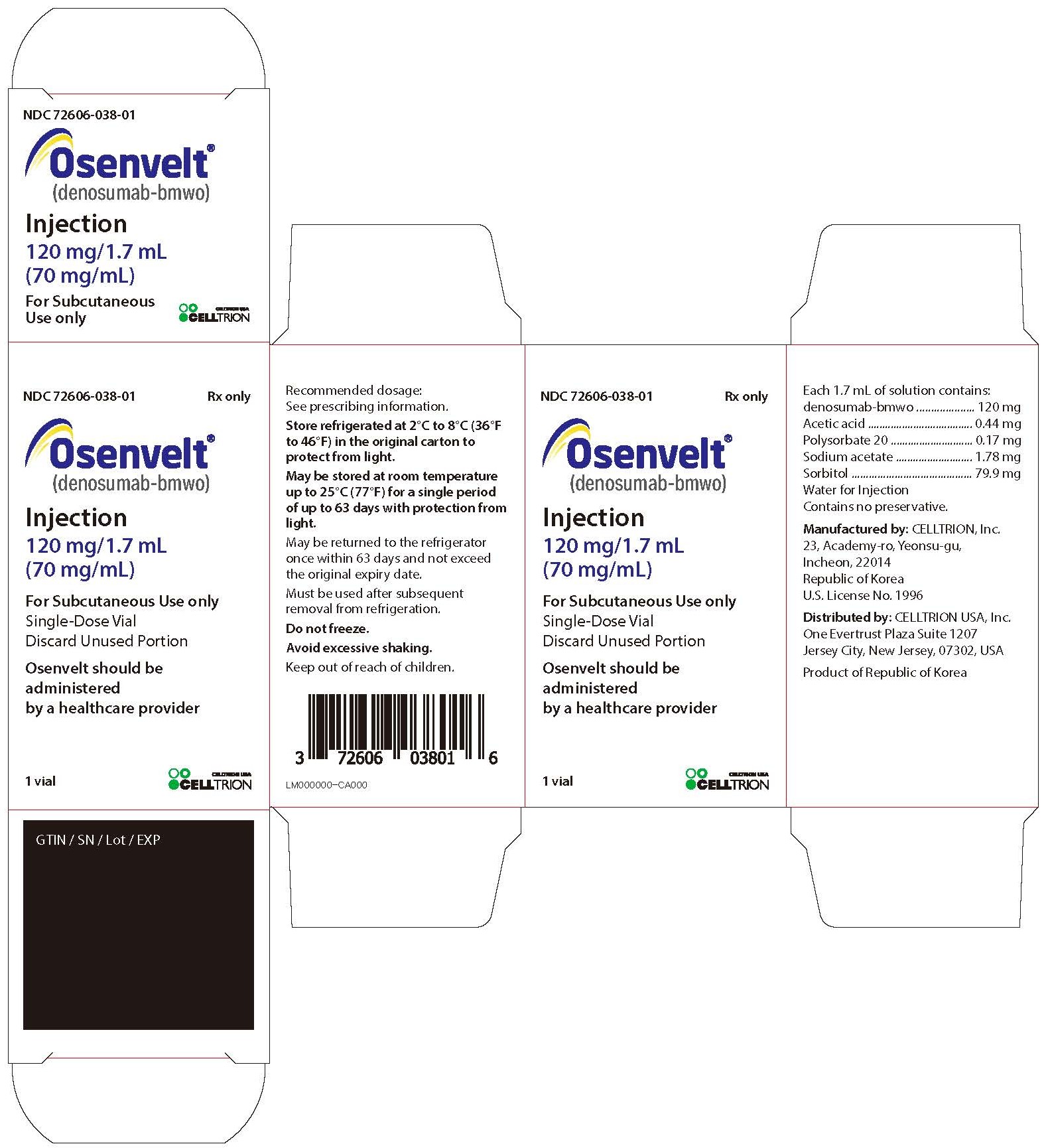 DRUG LABEL: Osenvelt
NDC: 72606-038 | Form: INJECTION
Manufacturer: CELLTRION USA, Inc.
Category: prescription | Type: HUMAN PRESCRIPTION DRUG LABEL
Date: 20260120

ACTIVE INGREDIENTS: DENOSUMAB 120 mg/1.7 mL
INACTIVE INGREDIENTS: SODIUM ACETATE 1.78 mg/1.7 mL; ACETIC ACID 0.44 mg/1.7 mL; POLYSORBATE 20 0.17 mg/1.7 mL; SORBITOL 79.90 mg/1.7 mL; WATER

HIGHLIGHTS OF PRESCRIBING INFORMATION

These highlights do not include all the information needed to use OSENVELT safely and effectively. See full prescribing information for OSENVELT.
OSENVELT® (denosumab-bmwo) injection, for subcutaneous use
Initial U.S. Approval: 2025
OSENVELT® (denosumab-bmwo) is biosimilar [Biosimilar means that the biological product is approved based on data demonstrating that it is highly similar to an FDA-approved biological product, known as a reference product, and that there are no clinically meaningful differences between the biosimilar product and the reference product. Biosimilarity of Osenvelt has been demonstrated for the condition(s) of use (e.g., indication(s), dosing regimen(s)), strength(s), dosage form(s), and route(s) of administration described in its Full Prescribing Information.] to XGEVA® (denosumab)

1 INDICATIONS AND USAGE

Osenvelt is a RANK ligand (RANKL) inhibitor indicated for:

- Prevention of skeletal-related events in patients with multiple myeloma and in patients with bone metastases from solid tumors. (1.1)
- Treatment of adults and skeletally mature adolescents with giant cell tumor of bone that is unresectable or where surgical resection is likely to result in severe morbidity. (1.2, 14.3)
- Treatment of hypercalcemia of malignancy refractory to bisphosphonate therapy. (1.3)

2 DOSAGE AND ADMINISTRATION

- Osenvelt should be administered by a healthcare provider. (2.1)
- Osenvelt is intended for subcutaneous route only and should not be administered intravenously, intramuscularly, or intradermally. (2.1)
- Multiple Myeloma and Bone Metastasis from Solid Tumors: Administer 120 mg every 4 weeks as a subcutaneous injection in the upper arm, upper thigh, or abdomen. (2.2)
- Giant Cell Tumor of Bone: Administer 120 mg every 4 weeks with additional 120 mg doses on Days 8 and 15 of the first month of therapy. Administer subcutaneously in the upper arm, upper thigh, or abdomen. (2.3)
- Administer calcium and vitamin D as necessary to treat or prevent hypocalcemia. (2.2, 2.3)
- Hypercalcemia of Malignancy: Administer 120 mg every 4 weeks with additional 120 mg doses on Days 8 and 15 of the first month of therapy. Administer subcutaneously in the upper arm, upper thigh, or abdomen. (2.4)

3 DOSAGE FORMS AND STRENGTHS

- Injection: 120 mg/1.7 mL (70 mg/mL) solution in a single-dose vial (3)

4 CONTRAINDICATIONS

- Hypocalcemia (4.1)
- Known clinically significant hypersensitivity to denosumab products (4.2)

5 WARNINGS AND PRECAUTIONS

- Drug Products with Same Active Ingredient: Patients receiving Osenvelt should not receive other denosumab products concomitantly. (5.1)
- Hypersensitivity reactions including anaphylaxis may occur. Discontinue permanently if a clinically significant reaction occurs. (5.2)
- Hypocalcemia: Denosumab products can cause severe symptomatic hypocalcemia. Fatal cases have been reported with denosumab products use. Correct hypocalcemia prior to initiating Osenvelt. Monitor calcium levels during therapy, especially in the first weeks of initiating therapy, and adequately supplement all patients with calcium and vitamin D. (5.3)
- Osteonecrosis of the jaw (ONJ) has been reported in patients receiving denosumab products. Perform an oral examination prior to starting Osenvelt. Monitor for symptoms. Avoid invasive dental procedures during treatment with Osenvelt. (5.4)
- Atypical femoral fracture: Evaluate patients with thigh or groin pain to rule out a femoral fracture. (5.5)
- Hypercalcemia Following Treatment Discontinuation in Patients with Giant Cell Tumor of Bone and in Patients with Growing Skeletons: Monitor patients for signs and symptoms of hypercalcemia, and manage as clinically appropriate. (5.6, 8.4)
- Multiple Vertebral Fractures (MVF) Following Treatment Discontinuation: When Osenvelt treatment is discontinued, evaluate the individual patient's risk for vertebral fractures. (5.7)
- Embryo-Fetal Toxicity: Can cause fetal harm. Advise females of reproductive potential of potential risk to the fetus and to use effective contraception. (5.8, 8.1, 8.3)

6 ADVERSE REACTIONS

- Bone Metastasis from Solid Tumors: Most common adverse reactions (≥ 25%) were fatigue/asthenia, hypophosphatemia, and nausea. (6.1)
- Multiple Myeloma: Most common adverse reactions (≥ 10%) were diarrhea, nausea, anemia, back pain, thrombocytopenia, peripheral edema, hypocalcemia, upper respiratory tract infection, rash, and headache. (6.1)
- Giant Cell Tumor of Bone: Most common adverse reactions (≥ 10%) were arthralgia, headache, nausea, back pain, fatigue, and pain in extremity. (6.1)
- Hypercalcemia of Malignancy: Most common adverse reactions (> 20%) were nausea, dyspnea, decreased appetite, headache, peripheral edema, vomiting, anemia, constipation, and diarrhea. (6.1)

To report SUSPECTED ADVERSE REACTIONS, contact CELLTRION USA, Inc. at 1-800-560-9414 or FDA at 1-800-FDA-1088 or www.fda.gov/medwatch.

8 USE IN SPECIFIC POPULATIONS

- Pediatric patients: Recommended only for treatment of skeletally mature adolescents with giant cell tumor of bone. (8.4)
- Renal impairment: Patients with creatinine clearance less than 30 mL/min or receiving dialysis are at risk for hypocalcemia. Adequately supplement with calcium and vitamin D. (8.6)

FULL PRESCRIBING INFORMATION

1 INDICATIONS AND USAGE

1.1 Multiple Myeloma and Bone Metastasis from Solid Tumors

Osenvelt is indicated for the prevention of skeletal-related events in patients with multiple myeloma and in patients with bone metastases from solid tumors.

1.2 Giant Cell Tumor of Bone

Osenvelt is indicated for the treatment of adults and skeletally mature adolescents with giant cell tumor of bone that is unresectable or where surgical resection is likely to result in severe morbidity [see Clinical Trials (14.2)].

1.3 Hypercalcemia of Malignancy

Osenvelt is indicated for the treatment of hypercalcemia of malignancy refractory to bisphosphonate therapy.

2 DOSAGE AND ADMINISTRATION

2.1 Important Administration Instructions

Osenvelt should be administered by a healthcare provider.

Osenvelt is intended for subcutaneous route only and should not be administered intravenously, intramuscularly, or intradermally.

2.2 Multiple Myeloma and Bone Metastasis from Solid Tumors

The recommended dose of Osenvelt is 120 mg administered as a subcutaneous injection every 4 weeks in the upper arm, upper thigh, or abdomen.

Administer calcium and vitamin D as necessary to treat or prevent hypocalcemia [see Warnings and Precautions (5.3)].

2.3 Giant Cell Tumor of Bone

The recommended dose of Osenvelt is 120 mg administered every 4 weeks with additional 120 mg doses on Days 8 and 15 of the first month of therapy. Administer subcutaneously in the upper arm, upper thigh, or abdomen.

Administer calcium and vitamin D as necessary to treat or prevent hypocalcemia [see Warnings and Precautions (5.3)].

2.4 Hypercalcemia of Malignancy

The recommended dose of Osenvelt is 120 mg administered every 4 weeks with additional 120 mg doses on Days 8 and 15 of the first month of therapy. Administer subcutaneously in the upper arm, upper thigh, or abdomen.

2.5 Preparation and Administration

Parenteral drug products should be inspected visually for particulate matter and discoloration prior to administration. Osenvelt is a clear, colorless to pale yellow solution. Do not use if the solution is discolored or cloudy or if the solution contains particles or foreign particulate matter.

Prior to administration, Osenvelt may be removed from the refrigerator and brought to room temperature up to 25°C (77°F) by standing in the original carton. This generally takes 15 to 30 minutes. Do not warm Osenvelt in any other way [see How Supplied/Storage and Handling (16)].

Use a 27-gauge needle to withdraw and inject the entire contents of the vial. Do not re-enter the vial. Discard vial after single-dose or entry.

3 DOSAGE FORMS AND STRENGTHS

Injection: 120 mg/1.7 mL (70 mg/mL) of clear, colorless to pale yellow solution in a single-dose vial.

4 CONTRAINDICATIONS

4.1 Hypocalcemia

Pre-existing hypocalcemia must be corrected prior to initiating therapy with Osenvelt [see Warnings and Precautions (5.3)].

4.2 Hypersensitivity

Osenvelt is contraindicated in patients with known clinically significant hypersensitivity to denosumab products [see Warnings and Precautions (5.2) and Adverse Reactions (6.2)].

5 WARNINGS AND PRECAUTIONS

5.1 Drug Products with Same Active Ingredient

Patients receiving Osenvelt should not receive other denosumab products concomitantly.

5.2 Hypersensitivity

Clinically significant hypersensitivity including anaphylaxis has been reported with use of denosumab products. Reactions may include hypotension, dyspnea, upper airway edema, lip swelling, rash, pruritus, and urticaria. If an anaphylactic or other clinically significant allergic reaction occurs, initiate appropriate therapy and discontinue Osenvelt therapy permanently [see Contraindications (4.2) and Adverse Reactions (6.2)].

5.3 Hypocalcemia

Denosumab products can cause severe symptomatic hypocalcemia, and fatal cases have been reported. Correct pre-existing hypocalcemia prior to Osenvelt treatment. Monitor calcium levels, throughout Osenvelt therapy, especially in the first weeks of initiating therapy, and administer calcium, magnesium, and vitamin D as necessary. Concomitant use of calcimimetics and other drugs that can lower calcium levels may worsen hypocalcemia risk and serum calcium should be closely monitored. Advise patients to contact a healthcare provider for symptoms of hypocalcemia [see Contraindications (4.1), Adverse Reactions (6.1, 6.2), and Patient Counseling Information (17)].

An increased risk of hypocalcemia has been observed in clinical trials of patients with increasing renal dysfunction, most commonly with severe dysfunction (creatinine clearance less than 30 mL/min and/or on dialysis), and with inadequate/no calcium supplementation. Monitor calcium levels and calcium and vitamin D intake [see Adverse Reactions (6.1), Use in Specific Populations (8.6), and Clinical Pharmacology (12.3)].

5.4 Osteonecrosis of the Jaw (ONJ)

Osteonecrosis of the jaw (ONJ) has been reported in patients receiving denosumab products, manifesting as jaw pain, osteomyelitis, osteitis, bone erosion, tooth or periodontal infection, toothache, gingival ulceration, or gingival erosion. Persistent pain or slow healing of the mouth or jaw after dental surgery may also be manifestations of ONJ. In clinical trials in patients with cancer, the incidence of ONJ was higher with longer duration of exposure [see Adverse Reactions (6.1)]. Seventy-nine percent of patients with ONJ had a history of tooth extraction, poor oral hygiene, or use of a dental appliance as a predisposing factor.

Other risk factors for the development of ONJ include immunosuppressive therapy, treatment with angiogenesis inhibitors, systemic corticosteroids, diabetes, and gingival infections. Similarly, for denosumab-treated patients with multiple myeloma that developed ONJ, 58% had a history of invasive dental procedures as a predisposing factor.

Perform an oral examination and appropriate preventive dentistry prior to the initiation of Osenvelt and periodically during Osenvelt therapy. Advise patients regarding oral hygiene practices. Avoid invasive dental procedures during treatment with Osenvelt. Consider temporary discontinuation of Osenvelt therapy if an invasive dental procedure must be performed. There are no data available to suggest the optimal duration of treatment interruption.

Patients who are suspected of having or who develop ONJ while on Osenvelt should receive care by a dentist or an oral surgeon. In these patients, extensive dental surgery to treat ONJ may exacerbate the condition. Clinical judgment of the treating healthcare provider should guide the management plan of each patient based on individual risk/benefit assessment.

5.5 Atypical Subtrochanteric and Diaphyseal Femoral Fracture

Atypical femoral fracture has been reported with denosumab products [see Adverse Reactions (6.1)]. These fractures can occur anywhere in the femoral shaft from just below the lesser trochanter to above the supracondylar flare and are transverse or short oblique in orientation without evidence of comminution.

Atypical femoral fractures most commonly occur with minimal or no trauma to the affected area. They may be bilateral and many patients report prodromal pain in the affected area, usually presenting as dull, aching thigh pain, weeks to months before a complete fracture occurs. A number of reports note that patients were also receiving treatment with glucocorticoids (e.g., prednisone) at the time of fracture.

During Osenvelt treatment, patients should be advised to report new or unusual thigh, hip, or groin pain. Any patient who presents with thigh or groin pain should be suspected of having an atypical fracture and should be evaluated to rule out an incomplete femur fracture. Patient presenting with an atypical femur fracture should also be assessed for symptoms and signs of fracture in the contralateral limb. Interruption of Osenvelt therapy should be considered, pending a risk/benefit assessment, on an individual basis.

5.6 Hypercalcemia Following Treatment Discontinuation in Patients with Giant Cell Tumor of Bone and in Patients with Growing Skeletons

Clinically significant hypercalcemia requiring hospitalization and complicated by acute renal injury has been reported in denosumab product-treated patients with giant cell tumor of bone and patients with growing skeletons. Hypercalcemia has been reported within the first year after treatment discontinuation. After treatment is discontinued, monitor patients for signs and symptoms of hypercalcemia, assess serum calcium periodically, reevaluate the patient's calcium and vitamin D supplementation requirements and manage patients as clinically appropriate [see Adverse Reactions (6) and Use in Specific Populations (8.4)].

5.7 Multiple Vertebral Fractures (MVF) Following Treatment Discontinuation

Multiple vertebral fractures (MVF) have been reported following discontinuation of treatment with denosumab products. Patients at higher risk for MVF include those with risk factors for or a history of osteoporosis or prior fractures.

When Osenvelt treatment is discontinued, evaluate the individual patient's risk for vertebral fractures [see Patient Counseling Information (17)].

5.8 Embryo-Fetal Toxicity

Based on data from animal studies and its mechanism of action, denosumab products can cause fetal harm when administered to a pregnant woman. In animal reproduction studies, administration of denosumab to cynomolgus monkeys throughout pregnancy at a dose 25-fold higher than the recommended human dose of denosumab based on body weight resulted in increased fetal loss, stillbirths, and postnatal mortality, along with evidence of absent peripheral lymph nodes, abnormal bone growth and decreased neonatal growth.

Verify the pregnancy status of females of reproductive potential prior to the initiation of Osenvelt. Advise pregnant women and females of reproductive potential that exposure to Osenvelt during pregnancy or within 5 months prior to conception can result in fetal harm. Advise females of reproductive potential to use effective contraception during therapy, and for at least 5 months after the last dose of Osenvelt [see Use in Specific Populations (8.1, 8.3) and Clinical Pharmacology (12.1)].

6 ADVERSE REACTIONS

The following adverse reactions are discussed below and elsewhere in the labeling:

- Hypersensitivity [see Warnings and Precautions (5.2)]
- Hypocalcemia [see Warnings and Precautions (5.3) and Use in Specific Populations (8.6)]
- Osteonecrosis of the Jaw [see Warnings and Precautions (5.4)]
- Atypical Subtrochanteric and Diaphyseal Femoral Fracture [see Warnings and Precautions (5.5)]
- Hypercalcemia following treatment discontinuation in patients with giant cell tumor of bone and in patients with growing skeletons [see Warnings and Precautions (5.6) and Use in Specific Populations (8.4)]
- Multiple vertebral fractures (MVF) following treatment discontinuation [see Warnings and Precautions (5.7)]

6.1 Clinical Trials Experience

Because clinical trials are conducted under widely varying conditions, adverse reaction rates observed in the clinical trials of a drug cannot be directly compared to rates in the clinical trials of another drug and may not reflect the rates observed in practice.

Bone Metastasis from Solid Tumors

The safety of denosumab was evaluated in three randomized, double-blind, double-dummy trials [see Clinical Trials (14.1)] in which a total of 2841 patients with bone metastasis from prostate cancer, breast cancer, or other solid tumors, or lytic bony lesions from multiple myeloma received at least one dose of denosumab. In Studies 20050136, 20050244, and 20050103, patients were randomized to receive either 120 mg of denosumab every 4 weeks as a subcutaneous injection or 4 mg (dose adjusted for reduced renal function) of zoledronic acid every 4 weeks by intravenous (IV) infusion. Entry criteria included serum calcium (corrected) from 8 to 11.5 mg/dL (2 to 2.9 mmol/L) and creatinine clearance 30 mL/min or greater. Patients who had received IV bisphosphonates were excluded, as were patients with prior history of ONJ or osteomyelitis of the jaw, an active dental or jaw condition requiring oral surgery, non-healed dental/oral surgery, or any planned invasive dental procedure. During the study, serum chemistries including calcium and phosphorus were monitored every 4 weeks. Calcium and vitamin D supplementation was recommended but not required.

The median duration of exposure to denosumab was 12 months (range: 0.1-41) and median duration on-study was 13 months (range: 0.1-41). Of patients who received denosumab, 46% were female. Eighty-five percent were White, 5% Hispanic/Latino, 6% Asian, and 3% Black. The median age was 63 years (range: 18-93). Seventy-five percent of patients who received denosumab received concomitant chemotherapy.

The most common adverse reactions in patients (incidence greater than or equal to 25%) were fatigue/asthenia, hypophosphatemia, and nausea (see Table 1). The most common serious adverse reaction was dyspnea. The most common adverse reactions resulting in discontinuation of denosumab were osteonecrosis and hypocalcemia.

Table 1. Selected [Adverse reactions reported in at least 10% of patients receiving denosumab in Studies 20050136, 20050244, and 20050103, and meeting one of the following criteria: - At least 1% greater incidence in denosumab-treated patients, or - Between-group difference (either direction) of less than 1% and more than 5% greater incidence in patients treated with zoledronic acid compared to placebo (US Prescribing Information for zoledronic acid)] Adverse Reactions of Any Severity (Studies 20050136, 20050244, and 20050103)
Body System | Denosumab n = 2841 % | Zoledronic Acid n = 2836 %
GASTROINTESTINAL
Nausea | 31 | 32
Diarrhea | 20 | 19
GENERAL
Fatigue/Asthenia | 45 | 46
INVESTIGATIONS
Hypocalcemia [Laboratory-derived and below the central laboratory lower limit of normal [8.3 - 8.5 mg/dL (2.075 - 2.125 mmol/L) for calcium and 2.2 - 2.8 mg/dL (0.71 - 0.9 mmol/L) for phosphorus]] | 18 | 9
Hypophosphatemia | 32 | 20
NEUROLOGICAL
Headache | 13 | 14
RESPIRATORY
Dyspnea | 21 | 18
Cough | 15 | 15

Severe Mineral/Electrolyte Abnormalities

- Severe hypocalcemia (corrected serum calcium less than 7 mg/dL or less than 1.75 mmol/L) occurred in 3.1% of patients treated with denosumab and 1.3% of patients treated with zoledronic acid. Of patients who experienced severe hypocalcemia, 33% experienced 2 or more episodes of severe hypocalcemia and 16% experienced 3 or more episodes [see Warnings and Precautions (5.3) and Use in Specific Populations (8.6)].
- Severe hypophosphatemia (serum phosphorus less than 2 mg/dL or less than 0.6 mmol/L) occurred in 15% of patients treated with denosumab and 7% of patients treated with zoledronic acid.

Osteonecrosis of the Jaw (ONJ)

In the primary treatment phases of Studies 20050136, 20050244, and 20050103, ONJ was confirmed in 1.8% of patients in the denosumab group (median exposure of 12.0 months; range: 0.1-41) and 1.3% of patients in the zoledronic acid group. The trials in patients with breast (Study 20050136) or prostate (Study 20050103) cancer included a denosumab open-label extension treatment phase where patients were offered denosumab 120 mg once every 4 weeks (median overall exposure of 14.9 months; range: 0.1-67.2). The patient-year adjusted incidence (number of events per 100 patient years) of confirmed ONJ was 1.1% during the first year of treatment, 3.7% in the second year, and 4.6% per year thereafter. The median time to ONJ was 20.6 months (range: 4-53) [see Warnings and Precautions (5.4)].

In a placebo-controlled clinical trial with an extension treatment phase evaluating denosumab for the prevention of bone metastases in patients with non-metastatic prostate cancer (a patient population for which denosumab is not indicated), with longer treatment exposure of up to 7 years, the patient-year adjusted incidence (number of events per 100 patient years) of confirmed ONJ was 1.1% during the first year of treatment, 3% in the second year, and 7% per year thereafter.

Atypical Subtrochanteric and Diaphyseal Fracture

In the clinical trial program, atypical femoral fracture has been reported in patients treated with denosumab and the risk increased with longer duration of treatment. Events have occurred during treatment and after treatment was discontinued [see Warnings and Precautions (5.5)].

Multiple Myeloma

The safety of denosumab was evaluated in an international, randomized (1:1), double-blind, active-controlled trial of patients with newly diagnosed multiple myeloma with treatment through disease progression [see Clinical Trials (14.2)]. In this trial, patients received 120 mg denosumab every 4 weeks as a subcutaneous injection (n = 850) or 4 mg (dose adjusted for renal function) of zoledronic acid intravenously (IV) every 4 weeks by IV infusion (n = 852). Entry criteria included serum calcium (corrected) from 8 to 11.5 mg/dL (2 to 2.9 mmol/L) and creatinine clearance 30 mL/min or greater. Patients who had received IV bisphosphonates were excluded, as were patients with prior history of ONJ or osteomyelitis of the jaw, an active dental or jaw condition requiring oral surgery, non-healed dental/oral surgery, or any planned invasive dental procedure. During the study, serum chemistries including calcium and phosphorus were monitored every 4 weeks. Calcium and vitamin D supplementation was recommended but not required.

The median duration of exposure to denosumab was 16 months (range: 1-50) and median duration on-study was 17 months (range: 0-49). Of patients who received denosumab, 46% were female, 83% were White, 13% Asian, 3% Black or African American, and 4% Hispanic/Latino. The median age of the patients randomized to denosumab was 63 years (range: 29-91) and all patients who received denosumab received concomitant anti-myeloma chemotherapy.

The adverse reaction profile of denosumab in patients with multiple myeloma, Study 20090482, was similar to that observed in Studies 20050136, 20050244, and 20050103. The most common adverse reactions (incidence ≥ 10%) were diarrhea (34%), nausea (32%), anemia (22%), back pain (21%), thrombocytopenia (19%), peripheral edema (17%), hypocalcemia (16%), upper respiratory tract infection (15%), rash (14%), and headache (11%). The most common serious adverse reaction (incidence ≥ 5%) was pneumonia (8%). The most common adverse reaction resulting in discontinuation of denosumab (≥ 1%) was osteonecrosis of the jaw.

Hypocalcemia and Hypophosphatemia

Severe hypocalcemia (corrected serum calcium less than 7 mg/dL or less than 1.75 mmol/L) and severe hypophosphatemia (serum phosphorus less than 2 mg/dL or less than 0.6 mmol/L) occurred in 2% and 21% patients treated with denosumab, respectively.

Osteonecrosis of the Jaw (ONJ)

In the primary treatment phase of Study 20090482, ONJ was confirmed in 4.1% of patients in the denosumab group (median exposure of 16 months; range: 1-50) and 2.8% of patients in the zoledronic acid group (median 15 months, range: 1-45 months). At the completion of the double-blind treatment phase of Study 20090482, the patient-year adjusted incidence (number of events per 100 patient years) of confirmed ONJ in the denosumab group (median exposure of 19.4 months; range: 1-52) was 2% during the first year of treatment, 5% in the second year, and 4.5% per year thereafter. The median time to ONJ was 18.7 months (range: 1-44) [see Warnings and Precautions (5.4)].

Giant Cell Tumor of Bone

The safety of denosumab was evaluated in two single-arm trials (Study 20062004 and Study 20040215) [see Clinical Trials (14.3)] in which a total of 548 adult or skeletally mature adolescent patients with giant cell tumor of bone received at least 1 dose of denosumab. Patients received 120 mg denosumab subcutaneously every 4 weeks with additional 120 mg doses on Days 8 and 15 of the first month of therapy. Patients receiving concurrent bisphosphonate therapy were excluded from enrollment in both studies. Patients with prior history of ONJ or osteomyelitis of the jaw, an active dental or jaw condition requiring oral surgery, non-healed dental/oral surgery, or any planned invasive dental procedure were excluded from enrollment in Study 20040215. During the trial, serum chemistries including calcium and phosphorus were monitored every 4 weeks. Calcium and vitamin D supplementation was recommended but not required.

Of the 548 patients who received denosumab, 467 patients were treated with denosumab for ≥ 1 year, 323 patients for ≥ 2 years, and 255 patients for ≥ 3 years. The median number of doses received was 33 (range: 4-138 doses) and the median number of months on-study was 60 (range: 0-140 months). Fifty-seven percent of the enrolled patients were women and 82% were White. The median age was 33 years (range: 13-83 years); a total of 19 patients were skeletally mature adolescents (12 to <17 years of age).

The common adverse reaction profile of denosumab in patients with giant cell tumor of bone was generally similar to that reported in Studies 20050136, 20050244, and 20050103. The most common adverse reactions in patients (incidence ≥ 10%) were arthralgia, back pain, pain in extremity, fatigue, headache, nausea, nasopharyngitis, musculoskeletal pain, toothache, vomiting, hypophosphatemia, constipation, diarrhea, and cough. The most frequent serious adverse reactions were osteonecrosis of the jaw (3.6%), bone giant cell tumor (1.5%), anemia (1.1%), pneumonia (0.9%), and back pain (0.9%). The most frequent adverse reactions resulting in discontinuation of denosumab was osteonecrosis of the jaw (incidence of 3.6%). The adverse reaction profile appeared similar in skeletally mature adolescents and adults.

Hypocalcemia and Hypophosphatemia

- Moderate to severe hypocalcemia (corrected serum calcium less than 8 mg/dL or less than 2 mmol/L) occurred in 5% of patients treated with denosumab.
- Severe hypophosphatemia (serum phosphorus less than 2 to 1 mg/dL or less than 0.6 to 0.3 mmol/L) occurred in 20% of patients treated with denosumab.

Osteonecrosis of the Jaw (ONJ)

In the pooled analysis of Study 20062004 and Study 20040215, ONJ was confirmed in 7% of patients who received denosumab (median number of doses received: 33; range: 4-138 doses).

Study 20140114 (NCT03301857) was a 5-year long term follow-up study for patients (n = 85) who completed Study 20062004. In Study 20062004 and Study 20140114 combined, ONJ was confirmed in 7% of patients who received denosumab (median time on trial 62.2 months (range 0 - 173). The combined patient-year adjusted incidence (number of events per 100 patient years) of confirmed ONJ was 0.2% during the first year of treatment, 1.5% in the second year, 1.8% in the third year, 2.1% in the fourth year, 1.4% in the fifth year, and 1.5% thereafter [see Warnings and Precautions (5.4)].

Atypical Subtrochanteric and Diaphyseal Fracture

In the pooled analysis of Study 20062004 and Study 20040215, atypical femoral fracture was observed in 0.9% of patients who received denosumab (median number of doses received: 33; range: 4-138 doses).

In Study 20062004 and Study 20140114, the combined incidence of confirmed atypical femoral fracture was 1.3% of patients who received denosumab [see Warnings and Precautions (5.5)].

Hypercalcemia Following Treatment Discontinuation

In the pooled safety population, 0.7% of patients experienced serious adverse events of hypercalcemia > 30 days following treatment discontinuation that was recurrent in some patients [see Warnings and Precautions (5.6)].

Hypercalcemia of Malignancy

Denosumab was evaluated in an open-label, single-arm trial (Study 20070315) in which 33 patients with hypercalcemia of malignancy (with or without bone metastases) refractory to treatment with intravenous bisphosphonate therapy were enrolled [see Clinical Trials (14.4)].

The adverse reaction profile of denosumab in patients with hypercalcemia of malignancy was similar to that reported in Studies 20050136, 20050244, 20050103, 20062004, and 20040215. Adverse reactions occurring in greater than 20% of patients were nausea (30%), dyspnea (27%), decreased appetite (24%), headache (24%), peripheral edema (24%), vomiting (24%), anemia (21%), constipation (21%), and diarrhea (21%). The following adverse reactions of Grade 3 or greater severity related to study therapy were reported on-study: fatigue (3%) and infection (6%). Grade 3 laboratory abnormalities included hypomagnesemia (3%), hypokalemia (3%), and hypophosphatemia (76%) of patients. No deaths on-study were related to denosumab therapy.

6.2 Postmarketing Experience

The following adverse reactions have been identified during post-approval use of denosumab products. Because these reactions are reported voluntarily from a population of uncertain size, it is not always possible to reliably estimate their frequency or establish a causal relationship to drug exposure.

- Hypocalcemia: Severe symptomatic hypocalcemia, including fatal cases [see Contraindications (4.1) and Warnings and Precautions (5.3)].
- Hypercalcemia: Severe symptomatic hypercalcemia following treatment discontinuation can occur [see Adverse Reactions (6) and Warnings and Precautions (5.6)].
- Hypersensitivity, including anaphylactic reactions [see Contraindications (4.2) and Warnings and Precautions (5.2)].
- Musculoskeletal pain, including severe musculoskeletal pain. Positive re-challenge has been reported.
- Lichenoid drug eruptions (e.g., lichen planus-like reactions).
- Alopecia.

8 USE IN SPECIFIC POPULATIONS

8.1 Pregnancy

Risk Summary

Based on findings in animals and its mechanism of action, denosumab products can cause fetal harm when administered to a pregnant woman [see Clinical Pharmacology (12.1)]. There are insufficient data with denosumab products use in pregnant women to inform any drug associated risks for adverse developmental outcomes. In utero denosumab exposure from cynomolgus monkeys dosed monthly with denosumab throughout pregnancy at a dose 25-fold higher than the recommended human dose of denosumab based on body weight resulted in increased fetal loss, stillbirths, and postnatal mortality; and absent lymph nodes, abnormal bone growth, and decreased neonatal growth [see Data].

Apprise pregnant women of the potential risk to the fetus.

The background rate of major birth defects and miscarriage is unknown for the indicated population. In the U.S. general population, the estimated background risk of major birth defects and miscarriage in clinically recognized pregnancies is 2-4% and 15-20%, respectively.

Data

Animal Data

The effects of denosumab on prenatal development have been studied in both cynomolgus monkeys and genetically engineered mice in which RANK ligand (RANKL) expression was turned off by gene removal (a "knockout mouse"). In cynomolgus monkeys dosed subcutaneously with denosumab throughout pregnancy starting at gestational day 20 and at a pharmacologically active dose 25-fold higher than the recommended human dose of denosumab based on body weight, there was increased fetal loss during gestation, stillbirths, and postnatal mortality. Other findings in offspring included absence of axillary, inguinal, mandibular, and mesenteric lymph nodes; abnormal bone growth, reduced bone strength, reduced hematopoiesis, dental dysplasia, and tooth malalignment; and decreased neonatal growth. At birth out to one month of age, infants had measurable blood levels of denosumab (22-621% of maternal levels).

Following a recovery period from birth out to 6 months of age, the effects on bone quality and strength returned to normal; there were no adverse effects on tooth eruption, though dental dysplasia was still apparent; axillary and inguinal lymph nodes remained absent, while mandibular and mesenteric lymph nodes were present, though small; and minimal to moderate mineralization in multiple tissues was seen in one recovery animal. There was no evidence of maternal harm prior to labor; adverse maternal effects occurred infrequently during labor. Maternal mammary gland development was normal. There was no fetal NOAEL (no observable adverse effect level) established for this study because only one dose of 50 mg/kg was evaluated. Mammary gland histopathology at 6 months of age was normal in female offspring exposed to denosumab in utero; however, development and lactation have not been fully evaluated.

In RANKL knockout mice, absence of RANKL (the target of denosumab) also caused fetal lymph node agenesis and led to postnatal impairment of dentition and bone growth. Pregnant RANKL knockout mice showed altered maturation of the maternal mammary gland, leading to impaired lactation [see Use in Specific Populations (8.3) and Nonclinical Toxicology (13.2)].

8.2 Lactation

Risk Summary

There is no information regarding the presence of denosumab products in human milk, the effects on the breastfed child, or the effects on milk production. Denosumab was detected in the maternal milk of cynomolgus monkeys up to 1 month after the last dose of denosumab (≤ 0.5% milk:serum ratio) and maternal mammary gland development was normal, with no impaired lactation. However, pregnant RANKL knockout mice showed altered maturation of the maternal mammary gland, leading to impaired lactation [see Use in Specific Populations (8.1) and Nonclinical Toxicology (13.2)]. Consider the developmental and health benefits of breastfeeding along with the mother's clinical need for Osenvelt treatment and any potential adverse effects on the breastfed child from Osenvelt or from the underlying maternal condition.

8.3 Females and Males of Reproductive Potential

Based on findings in animals and its mechanism of action, denosumab products can cause fetal harm when administered to a pregnant woman [see Use in Specific Populations (8.1)].

Pregnancy Testing

Verify the pregnancy status of females of reproductive potential prior to initiating Osenvelt treatment.

Contraception

Females

Advise females of reproductive potential to use effective contraception during therapy, and for at least 5 months after the last dose of Osenvelt.

8.4 Pediatric Use

The safety and efficacy of Osenvelt have not been established in pediatric patients except in skeletally mature adolescents (aged 12-16 years) with giant cell tumor of bone. Osenvelt is recommended only for treatment of skeletally mature adolescents (aged 12-16 years) with giant cell tumor of bone [see Indications and Usage (1.2)]. Clinically significant hypercalcemia after treatment discontinuation has been reported in pediatric patients with growing skeletons who received denosumab products for giant cell tumor of bone or for unapproved indications [see Adverse Reactions (6.2) and Warnings and Precautions (5.6)].

Denosumab was studied in an open-label trial that enrolled a subset of 19 adolescent patients (aged 12-16 years) with giant cell tumor of bone who had reached skeletal maturity, defined by at least 1 mature long bone (e.g., closed epiphyseal growth plate of the humerus), and had a body weight ≥ 45 kg [see Indications and Usage (1.2) and Clinical Trials (14.3)]. A total of one of five (20%) evaluable adolescent patients had an objective response by retrospective independent assessment of radiographic response according to modified Response Evaluation Criteria in Solid Tumors (RECIST 1.1). The adverse reaction profile and efficacy results appeared to be similar in skeletally mature adolescents and adults [see Adverse Reactions (6.1) and Clinical Trials (14.3)].

Animal Data

Treatment with denosumab products may impair bone growth in children with open growth plates and may inhibit eruption of dentition. In neonatal rats, inhibition of RANKL (the target of denosumab therapy) with a construct of osteoprotegerin bound to Fc (OPG-Fc) at doses ≤ 10 mg/kg was associated with inhibition of bone growth and tooth eruption. Adolescent primates treated with denosumab at doses 5 and 25 times (10 and 50 mg/kg dose) higher than the recommended human dose of 120 mg administered once every 4 weeks, based on body weight (mg/kg), had abnormal growth plates, considered to be consistent with the pharmacological activity of denosumab.

Cynomolgus monkeys exposed in utero to denosumab exhibited bone abnormalities, reduced hematopoiesis, tooth malalignment, decreased neonatal growth, and an absence of axillary, inguinal, mandibular, and mesenteric lymph nodes. Some bone abnormalities recovered once exposure was ceased following birth; however, axillary and inguinal lymph nodes remained absent 6 months post-birth [see Use in Specific Populations (8.1)].

8.5 Geriatric Use

Of the total number of patients in clinical studies that received denosumab (n = 2841) in Studies 20050136, 20050244, and 20050103, 1271 (44%) were ≥ 65 years old, while 473 patients (17%) were ≥ 75 years old. Of the 859 patients in Study 20090482 that received denosumab, 387 patients (45%) were ≥ 65 years old, while 141 patients (16%) were ≥ 75 years old. No overall differences in safety or efficacy were observed between older and younger patients.

8.6 Renal Impairment

Two clinical trials were conducted in patients without cancer and with varying degrees of renal function.

In one study, patients (N = 55) with varying degrees of renal function (ranging from normal through end-stage renal disease requiring dialysis) received a single 60 mg subcutaneous dose of denosumab. In a second study, patients (N = 32) with severe renal dysfunction (creatinine clearance less than 30 mL/min and/or on dialysis) were given two 120 mg subcutaneous doses of denosumab. In both studies, greater risk of developing hypocalcemia was observed with increasing renal impairment, and with inadequate/no calcium supplementation. Hypocalcemia was mild to moderate in severity in 96% of patients. Monitor calcium levels and calcium and vitamin D intake [see Warnings and Precautions (5.3), Adverse Reactions (6.1), and Clinical Pharmacology (12.3)].

10 OVERDOSAGE

There is no experience with overdosage of denosumab products.

11 DESCRIPTION

Denosumab-bmwo is a human IgG2 monoclonal antibody that binds to human RANKL.

Denosumab-bmwo has an approximate molecular weight of 147 kDa and is produced in genetically engineered mammalian (Chinese hamster ovary) cells.

Osenvelt (denosumab-bmwo) injection is a sterile, preservative-free, clear, colorless to pale yellow solution for subcutaneous use.

Each single-dose vial of Osenvelt contains 120 mg denosumab-bmwo, 0.44 mg acetic acid, 0.17 mg polysorbate 20, 1.78 mg sodium acetate, 79.9 mg sorbitol, and Water for Injection. The pH is 5.2.

12 CLINICAL PHARMACOLOGY

12.1 Mechanism of Action

Denosumab products bind to RANKL, a transmembrane or soluble protein essential for the formation, function, and survival of osteoclasts, the cells responsible for bone resorption, thereby modulating calcium release from bone. Increased osteoclast activity, stimulated by RANKL, is a mediator of bone pathology in solid tumors with osseous metastases. Similarly, giant cell tumors of bone consist of stromal cells expressing RANKL and osteoclast-like giant cells expressing RANK receptor, and signaling through the RANK receptor contributes to osteolysis and tumor growth. Denosumab products prevent RANKL from activating its receptor, RANK, on the surface of osteoclasts, their precursors, and osteoclast-like giant cells.

12.2 Pharmacodynamics

In patients with breast cancer and bone metastases, the median reduction in uNTx/Cr was 82% within 1 week following initiation of denosumab 120 mg administered subcutaneously. In Studies 20050136, 20050244, and 20050103, the median reduction in uNTx/Cr from baseline to Month 3 was approximately 80% in 2075 denosumab-treated patients.

In a phase 3 study of patients with newly diagnosed multiple myeloma who received subcutaneous doses of denosumab 120 mg every 4 weeks (Q4W), median reductions in uNTx/Cr of approximately 75% were observed by week 5. Reductions in bone turnover markers were maintained, with median reductions of 74% to 79% for uNTx/Cr from weeks 9 to 49 of continued 120 mg Q4W dosing.

In adult and skeletally mature adolescent patients with giant cell tumor of bone who received subcutaneous doses of denosumab 120 mg Q4W with a 120 mg loading dose on Days 8 and 15, median reductions in uNTx/Cr from baseline were 84% at Week 13 and 82% at Week 25.

12.3 Pharmacokinetics

Following subcutaneous administration, bioavailability was 62%. Denosumab displayed nonlinear pharmacokinetics at doses below 60 mg, but approximately dose-proportional increases in exposure at higher doses.

With multiple subcutaneous doses of 120 mg once every 4 weeks, up to 2.8-fold accumulation in serum denosumab concentrations was observed and steady-state was achieved by 6 months. A mean (± standard deviation) serum steady-state trough concentration of 20.5 (± 13.5) mcg/mL was achieved by 6 months. The mean elimination half-life was 28 days.

In patients with newly diagnosed multiple myeloma who received 120 mg every 4 weeks, denosumab concentrations appear to reach steady-state by month 6. In patients with giant cell tumor of bone, after administration of subcutaneous doses of 120 mg once every 4 weeks with additional 120 mg doses on Days 8 and 15 of the first month of therapy, mean (± standard deviation) serum trough concentrations on Day 8, 15, and one month after the first dose were 19.0 (± 24.1), 31.6 (± 27.3), 36.4 (± 20.6) mcg/mL, respectively. Steady-state was achieved in 3 months after initiation of treatment with a mean serum trough concentration of 23.4 (± 12.1) mcg/mL.

Special Populations

Body Weight: A population pharmacokinetic analysis was performed to evaluate the effects of demographic characteristics. Denosumab clearance and volume of distribution were proportional to body weight. The steady-state exposure following repeat subcutaneous administration of 120 mg every 4 weeks to 45 kg and 120 kg subjects were, respectively, 48% higher and 46% lower than exposure of the typical 66 kg subject.

Age, Gender and Race: The pharmacokinetics of denosumab was not affected by age, gender, and race.

Pediatrics: In skeletally-mature adolescent patients (12 to 16 years of age) with giant cell tumor of bone (GCTB) who received 120 mg every 4 weeks with a 120 mg loading dose on Days 8 and 15, the pharmacokinetics of denosumab were comparable to those observed in adult patients with GCTB.

Hepatic Impairment: No clinical trials have been conducted to evaluate the effect of hepatic impairment on the pharmacokinetics of denosumab products.

Renal Impairment: In clinical trials of 87 patients with varying degrees of renal dysfunction, including patients on dialysis, the degree of renal impairment had no effect on the pharmacokinetics and pharmacodynamics of denosumab [see Use in Specific Populations (8.6)].

Drug Interactions

No formal drug-drug interaction trials have been conducted with denosumab. There was no evidence that various anticancer treatments affected denosumab systemic exposure and pharmacodynamic effect. Serum denosumab concentrations at 1 and 3 months and reductions in the bone turnover marker uNTx/Cr (urinary N-terminal telopeptide corrected for creatinine) at 3 months were similar in patients with and without prior intravenous bisphosphonate therapy and were not altered by concomitant chemotherapy and/or hormone therapy.

12.6 Immunogenicity

The observed incidence of anti-drug antibodies is highly dependent on the sensitivity and specificity of the assay. Differences in assay methods preclude meaningful comparisons of the incidence of anti-drug antibodies in the studies described below with the incidence of anti-drug antibodies in other studies, including those of denosumab or of other denosumab products. Using an electrochemiluminescent bridging immunoassay, less than 1% (55 out of 8113) of patients treated with denosumab for up to 5 years tested positive for binding antibodies (including pre-existing, transient, and developing antibodies). None of the patients tested positive for neutralizing antibodies, as was assessed using a chemiluminescent cell-based in vitro biological assay. There was no identified clinically significant effect of anti-drug antibodies on pharmacokinetics, pharmacodynamics, safety, or effectiveness of denosumab.

13 NONCLINICAL TOXICOLOGY

13.1 Carcinogenesis, Mutagenesis, Impairment of Fertility

Carcinogenicity

The carcinogenic potential of denosumab products has not been evaluated in long-term animal studies.

Mutagenicity

The genotoxic potential of denosumab products has not been evaluated.

Impairment of Fertility

Denosumab had no effect on female fertility or male reproductive organs in monkeys at doses that were 6.5- to 25-fold higher than the recommended human dose of 120 mg subcutaneously administered once every 4 weeks, based on body weight (mg/kg).

13.2 Animal Toxicology and/or Pharmacology

Denosumab products are inhibitors of osteoclastic bone resorption via inhibition of RANKL.

Because the biological activity of denosumab in animals is specific to nonhuman primates, evaluation of genetically engineered (knockout) mice or use of other biological inhibitors of the RANK/RANKL pathway, OPG-Fc and RANK-Fc, provided additional information on the pharmacodynamic properties of denosumab. RANK/RANKL knockout mice exhibited absence of lymph node formation, as well as an absence of lactation due to inhibition of mammary gland maturation (lobulo-alveolar gland development during pregnancy). Neonatal RANK/RANKL knockout mice exhibited reduced bone growth and lack of tooth eruption. A corroborative study in 2-week-old rats given the RANKL inhibitor OPG-Fc also showed reduced bone growth, altered growth plates, and impaired tooth eruption. These changes were partially reversible in this model when dosing with the RANKL inhibitors was discontinued.

14 CLINICAL TRIALS

14.1 Bone Metastasis from Solid Tumors

The safety and efficacy of denosumab for the prevention of skeletal-related events in patients with bone metastases from solid tumors was demonstrated in three international, randomized (1:1), double-blind, active-controlled, noninferiority trials comparing denosumab with zoledronic acid. In all three trials, patients were randomized to receive 120 mg denosumab subcutaneously every 4 weeks or 4 mg zoledronic acid intravenously (IV) every 4 weeks (dose adjusted for reduced renal function). Patients with creatinine clearance less than 30 mL/min were excluded. In each trial, the main outcome measure was demonstration of noninferiority of time to first skeletal-related event (SRE) as compared to zoledronic acid. Supportive outcome measures were superiority of time to first SRE and superiority of time to first and subsequent SRE; testing for these outcome measures occurred if the main outcome measure was statistically significant. An SRE was defined as any of the following: pathologic fracture, radiation therapy to bone, surgery to bone, or spinal cord compression.

Study 20050136 (NCT00321464) enrolled 2046 patients with advanced breast cancer and bone metastasis. Randomization was stratified by a history of prior SRE (yes or no), receipt of chemotherapy within 6 weeks prior to randomization (yes or no), prior oral bisphosphonate use (yes or no), and region (Japan or other countries). Forty percent of patients had a previous SRE, 40% received chemotherapy within 6 weeks prior to randomization, 5% received prior oral bisphosphonates, and 7% were enrolled from Japan. Median age was 57 years, 80% of patients were White, and 99% of patients were women. The median number of doses administered was 18 for denosumab and 17 for zoledronic acid.

Study 20050244 (NCT00330759) enrolled 1776 adults with solid tumors other than breast and castrate-resistant prostate cancer with bone metastasis and multiple myeloma. Randomization was stratified by previous SRE (yes or no), systemic anticancer therapy at time of randomization (yes or no), and tumor type (non-small cell lung cancer, myeloma, or other). Eighty-seven percent were receiving systemic anticancer therapy at the time of randomization, 52% had a previous SRE, 64% of patients were men, 87% were White, and the median age was 60 years. A total of 40% of patients had non-small cell lung cancer, 10% had multiple myeloma, 9% had renal cell carcinoma, and 6% had small cell lung cancer. Other tumor types each comprised less than 5% of the enrolled population. The median number of doses administered was 7 for both denosumab and zoledronic acid.

Study 20050103 (NCT00321620) enrolled 1901 men with castrate-resistant prostate cancer and bone metastasis. Randomization was stratified by previous SRE, PSA level (less than 10 ng/mL or 10 ng/mL or greater) and receipt of chemotherapy within 6 weeks prior to randomization (yes or no). Twenty-six percent of patients had a previous SRE, 15% of patients had PSA less than 10 ng/mL, and 14% received chemotherapy within 6 weeks prior to randomization. Median age was 71 years and 86% of patients were White. The median number of doses administered was 13 for denosumab and 11 for zoledronic acid.

Denosumab delayed the time to first SRE following randomization as compared to zoledronic acid in patients with breast or castrate-resistant prostate cancer (CRPC) with osseous metastases (Table 2). In patients with bone metastasis due to other solid tumors or lytic lesions due to multiple myeloma, denosumab was noninferior to zoledronic acid in delaying the time to first SRE following randomization.

Overall survival and progression-free survival were similar between arms in all three trials.

Table 2. Efficacy Results for Denosumab Compared to Zoledronic Acid
 | Study 20050136 Metastatic Breast Cancer |  | Study 20050244 Metastatic Solid Tumors or Multiple Myeloma |  | Study 20050103 Metastatic CRPC [CRPC = castrate-resistant prostate cancer.]
 | Denosumab N = 1026 | Zoledronic Acid N = 1020 | Denosumab N = 886 | Zoledronic Acid N = 890 | Denosumab N = 950 | Zoledronic Acid N = 951
First On-study SRE
Number of Patients who had SREs (%) | 315 (30.7) | 372 (36.5) | 278 (31.4) | 323 (36.3) | 341 (35.9) | 386 (40.6)
Components of First SRE
Radiation to Bone | 82 (8.0) | 119 (11.7) | 119 (13.4) | 144 (16.2) | 177 (18.6) | 203 (21.3)
Pathological Fracture | 212 (20.7) | 238 (23.3) | 122 (13.8) | 139 (15.6) | 137 (14.4) | 143 (15.0)
Surgery to Bone | 12 (1.2) | 8 (0.8) | 13 (1.5) | 19 (2.1) | 1 (0.1) | 4 (0.4)
Spinal Cord Compression | 9 (0.9) | 7 (0.7) | 24 (2.7) | 21 (2.4) | 26 (2.7) | 36 (3.8)
Median Time to SRE (months) | NR [NR = not reached.] | 26.4 | 20.5 | 16.3 | 20.7 | 17.1
Hazard Ratio (95% CI) | 0.82 (0.71, 0.95) |  | 0.84 (0.71, 0.98) |  | 0.82 (0.71, 0.95)
Noninferiority p-value | < 0.001 |  | < 0.001 |  | < 0.001
Superiority p-value [Superiority testing performed only after denosumab demonstrated to be noninferior to zoledronic acid within trial.] | 0.010 |  | 0.060 |  | 0.008
First and Subsequent SRE [All skeletal events postrandomization; new events defined by occurrence ≥ 21 days after preceding event.]
Mean Number/Patient | 0.46 | 0.60 | 0.44 | 0.49 | 0.52 | 0.61
Rate Ratio (95% CI) | 0.77 (0.66, 0.89) |  | 0.90 (0.77, 1.04) |  | 0.82 (0.71, 0.94)
Superiority p-value [Adjusted p-values are presented.] | 0.001 |  | 0.145 |  | 0.009

14.2 Multiple Myeloma

The efficacy of denosumab for the prevention of skeletal-related events in newly diagnosed multiple myeloma patients with treatment through disease progression, was evaluated in Study 20090482 (NCT01345019), an international, randomized (1:1), double-blind, active-controlled, noninferiority trial comparing denosumab with zoledronic acid. In this trial, patients were randomized to receive 120 mg denosumab subcutaneously every 4 weeks or 4 mg zoledronic acid intravenously (IV) every 4 weeks (dose adjusted for reduced renal function). Patients with creatinine clearance less than 30 mL/min were excluded. In this trial, the main efficacy outcome measure was noninferiority of time to first skeletal-related event (SRE). Additional efficacy outcome measures were superiority of time to first SRE, time to first and subsequent SRE, and overall survival. An SRE was defined as any of the following: pathologic fracture, radiation therapy to bone, surgery to bone, or spinal cord compression.

Study 20090482 enrolled 1718 newly diagnosed multiple myeloma patients with bone lesions. Randomization was stratified by a history of prior SRE (yes or no), the anti-myeloma agent being utilized/planned to be utilized in first-line therapy (novel therapy-based or non-novel therapy-based [novel therapies include bortezomib, lenalidomide, or thalidomide]), intent to undergo autologous PBSC transplantation (yes or no), stage at diagnosis (International Staging System I or II or III) and region Japan (yes or no). At study enrollment, 96% of the patients were receiving or planning to receive novel therapy-based first-line anti-myeloma therapy, 55% of the patients intended to undergo autologous PBSC transplantation, 61% of patients had a previous SRE, 32% were at ISS stage I, 38% were at ISS stage II and 29% were at ISS Stage III, and 2% were enrolled from Japan. Median age was 63 years, 82% of patients were White, and 46% of patients were women. The median number of doses administered was 16 for denosumab and 15 for zoledronic acid.

Denosumab was noninferior to zoledronic acid in delaying the time to first SRE following randomization (HR = 0.98, 95% CI, 0.85-1.14). The results for overall survival (OS) were comparable between denosumab and zoledronic acid treatment groups with a hazard ratio of 0.90 (95% CI: 0.70, 1.16).

Table 3. Efficacy Results for Denosumab Compared to Zoledronic Acid
 | Study 20090482 Multiple Myeloma
 | Denosumab N = 859 | Zoledronic Acid N = 859
First On-study SRE
Number of Patients who had SREs (%) | 376 (43.8) | 383 (44.6)
Components of First SRE
Radiation to Bone | 47 (5.5) | 62 (7.2)
Pathological Fracture | 342 (39.8) | 338 (39.3)
Surgery to Bone | 37 (4.3) | 48 (5.6)
Spinal Cord Compression | 6 (0.7) | 4 (0.5)
Median Time to SRE (months) (95% CI) | 22.8 (14.7, NE [NE = not estimable]) | 24 (16.6, 33.3)
Hazard Ratio (95% CI) | 0.98 (0.85, 1.14)

14.3 Giant Cell Tumor of Bone

The safety and efficacy of denosumab for the treatment of giant cell tumor of bone in adults or skeletally mature adolescents were demonstrated in two open-label trials [Study 20040215 (NCT00396279) and Study 20062004 (NCT00680992)] that enrolled patients with histologically confirmed measurable giant cell tumor of bone that was either recurrent, unresectable, or for which planned surgery was likely to result in severe morbidity. Patients received 120 mg denosumab subcutaneously every 4 weeks with a loading dose on Days 8 and 15 of the first cycle of therapy. Patients who discontinued denosumab then entered the safety follow-up phase for a minimum of 60 months. Retreatment with denosumab while in safety follow-up was allowed for patients who initially demonstrated a response to denosumab (e.g., in the case of recurrent disease).

Study 20040215 was a single-arm, pharmacodynamic, and proof of concept trial conducted in 37 adult patients with unresectable or recurrent giant cell tumor of bone. Patients were required to have histologically confirmed giant cell tumor of bone and radiologic evidence of measurable disease from a computed tomography (CT) or magnetic resonance imaging (MRI) obtained within 28 days prior to study enrollment. Patients enrolled in Study 20040215 underwent CT or MRI assessment of giant cell tumor of bone at baseline and quarterly during denosumab treatment.

Study 20062004 was a parallel-cohort, proof of concept, and safety trial conducted in 535 adult or skeletally mature adolescent patients with histologically confirmed giant cell tumor of bone and evidence of measurable active disease. Study 20062004 enrolled 19 patients who were 12-16 years of age [see Use in Specific Populations (8.4)]. Patients enrolled into one of three cohorts: Cohort 1 enrolled 268 patients with surgically unsalvageable disease (e.g., sacral or spinal sites of disease, or pulmonary metastases); Cohort 2 enrolled 252 patients with surgically salvageable disease where the investigator determined that the planned surgery was likely to result in severe morbidity (e.g., joint resection, limb amputation, or hemipelvectomy); Cohort 3 enrolled 15 patients who previously participated in Study 20040215. Patients underwent imaging assessment of disease status at intervals determined by their treating physician.

A retrospective interim analysis concluded by an independent review committee evaluated objective response in 187 patients enrolled and treated in Study 20040215 and Study 20062004 for whom baseline and at least one post-baseline radiographic assessment were available (27 of 37 patients enrolled in Study 20040215 and 160 of 270 patients enrolled in Cohorts 1 and 2 of Study 20062004). The primary efficacy outcome measure was objective response rate using Response Evaluation Criteria in Solid Tumors (RECIST) v 1.1.

The overall objective response rate (RECIST 1.1) was 25% (95% CI: 19, 32). All responses were partial responses. The estimated median time to response was 3 months. In the 47 patients with an objective response, the median duration of follow-up was 20 months (range: 2-44 months), and 51% (24/47) had a duration of response lasting at least 8 months. Three patients experienced disease progression following an objective response.

14.4 Hypercalcemia of Malignancy

The safety and efficacy of denosumab was demonstrated in an open-label, single-arm trial [Study 20070315 (NCT00896454)] that enrolled 33 patients with hypercalcemia of malignancy (with or without bone metastases) refractory to treatment with intravenous bisphosphonate therapy. Patients received denosumab subcutaneously every 4 weeks with additional 120 mg doses on Days 8 and 15 of the first month of therapy.

In this trial, refractory hypercalcemia of malignancy was defined as an albumin-corrected calcium of > 12.5 mg/dL (3.1 mmol/L) despite treatment with intravenous bisphosphonate therapy in 7-30 days prior to initiation of denosumab therapy. The primary outcome measure was the proportion of patients achieving a response, defined as corrected serum calcium (CSC) ≤ 11.5 mg/dL (2.9 mmol/L), within 10 days after denosumab administration. Efficacy data are summarized in Figure 1 and Table 4. Concurrent chemotherapy did not appear to affect response to denosumab.

Figure 1. Corrected Serum Calcium by Visit in Responders (Median and Interquartile Range)

N = Number of responders who received ≥ 1 dose of investigational product
n = Number of responders who had no missing data at baseline and the time point of interest

Table 4. Efficacy in Patients with Hypercalcemia of Malignancy Refractory to Bisphosphonate Therapy
 | N = 33 | Proportion (%) (95% CI)
All Responders (CSC ≤ 11.5 mg/dL) by Day 10 | 21 | 63.6 (45.1, 79.6)
All Responders by Day 57 | 23 | 69.7 (51.3, 84.4)
Complete Responders (CSC ≤ 10.8 mg/dL) by Day 10 | 12 | 36.4 (20.4, 54.9)
All Complete Responders by Day 57 | 21 | 63.6 (45.1, 79.6)

Median time to response (CSC ≤ 11.5 mg/dL) was 9 days (95% CI: 8, 19), and the median duration of response was 104 days (95% CI: 7, not estimable). Median time to complete response (CSC ≤ 10.8 mg/dL) was 23 days (95% CI: 9, 36), and the median duration of complete response was 34 days (95% CI: 1, 134).

16 HOW SUPPLIED/STORAGE AND HANDLING

How Supplied

Osenvelt (denosumab-bmwo) injection is a clear, colorless to pale yellow solution supplied in a single-dose vial.

120 mg/1.7 mL (70 mg/mL) in a single-dose vial | 1 vial per carton | NDC 72606-038-01

Storage and Handling

Store Osenvelt refrigerated at 2°C to 8°C (36°F to 46°F) in the original carton to protect from light. Do not freeze. Prior to administration, Osenvelt may be allowed to reach room temperature up to 25°C (77°F) in the original carton. Osenvelt may be stored at temperatures up to a maximum 25°C (77°F) for a single period of up to 63 days but not exceeding the original expiry date. If necessary, the product may be returned to the refrigerator once within 63 days and provided this does not exceed the original expiry date. It must be used after subsequent removal from refrigeration. Discard Osenvelt if not used or returned to refrigerator within the 63 days. Do not use Osenvelt after the expiry date printed on the label.

Protect Osenvelt from direct light and heat. Avoid vigorous shaking of Osenvelt.

17 PATIENT COUNSELING INFORMATION

Drug Products with Same Active Ingredient

Advise patients that if they receive Osenvelt, they should not receive other denosumab products concomitantly [see Warnings and Precautions (5.1)].

Hypersensitivity

Advise patients to seek prompt medical attention if signs or symptoms of hypersensitivity reactions occur. Advise patients who have had signs or symptoms of systemic hypersensitivity reactions that they should not receive denosumab products [see Warnings and Precautions (5.2) and Contraindications (4.2)].

Hypocalcemia

Adequately supplement patients with calcium and vitamin D and instruct them on the importance of maintaining serum calcium levels while receiving Osenvelt [see Warnings and Precautions (5.3) and Use in Specific Populations (8.6)]. Advise patients to seek prompt medical attention if they develop signs or symptoms of hypocalcemia.

Osteonecrosis of the Jaw

Advise patients to maintain good oral hygiene during treatment with Osenvelt and to inform their dentist prior to dental procedures that they are receiving Osenvelt. Patients should avoid invasive dental procedures during treatment with Osenvelt and inform their healthcare provider or dentist if they experience persistent pain and/or slow healing of the mouth or jaw after dental surgery [see Warnings and Precautions (5.4)].

Atypical Subtrochanteric and Diaphyseal Femoral Fracture

Advise patients to report new or unusual thigh, hip, or groin pain [see Warnings and Precautions (5.5)].

Hypercalcemia Following Treatment Discontinuation in Patients with Giant Cell Tumor of Bone and in Patients with Growing Skeletons

Advise patients to report nausea, vomiting, headache, and decreased alertness following treatment discontinuation [see Warnings and Precautions (5.6) and Use in Specific Populations (8.4)].

Multiple Vertebral Fractures (MVF) Following Treatment Discontinuation

Advise patients that after treatment with Osenvelt is stopped there may be an increased risk of having broken bones in the spine especially in patients who have had a fracture or who have had osteoporosis. Advise patients not to interrupt Osenvelt therapy without their physician's advice [see Warnings and Precautions (5.7)].

Embryo-Fetal Toxicity

Advise females of reproductive potential that Osenvelt can cause harm to a fetus and to inform their healthcare provider of a known or suspected pregnancy [see Warnings and Precautions (5.8) and Use in Specific Populations (8.1, 8.3)].

Advise females of reproductive potential to use effective contraception during treatment and for at least 5 months after the last dose of Osenvelt [see Use in Specific Populations (8.3)].

OSENVELT® (denosumab-bmwo)

Manufactured by:
CELLTRION, Inc.
23, Academy-ro, Yeonsu-gu,
Incheon, 22014
Republic of Korea
U.S. License No. 1996

Distributed by:
CELLTRION USA, Inc.
One Evertrust Plaza Suite 1207,
Jersey City, New Jersey,
07302, USA

PRINCIPAL DISPLAY PANEL - 120 mg/1.7 mL Vial Carton

NDC 72606-038-01
Rx only

Osenvelt®
(denosumab-bmwo)

Injection
120 mg/1.7 mL
(70 mg/mL)

For Subcutaneous Use only
Single-Dose Vial
Discard Unused Portion

Osenvelt should be
administered
by a healthcare provider

1 vial

CELLTRION USA
CELLTRION